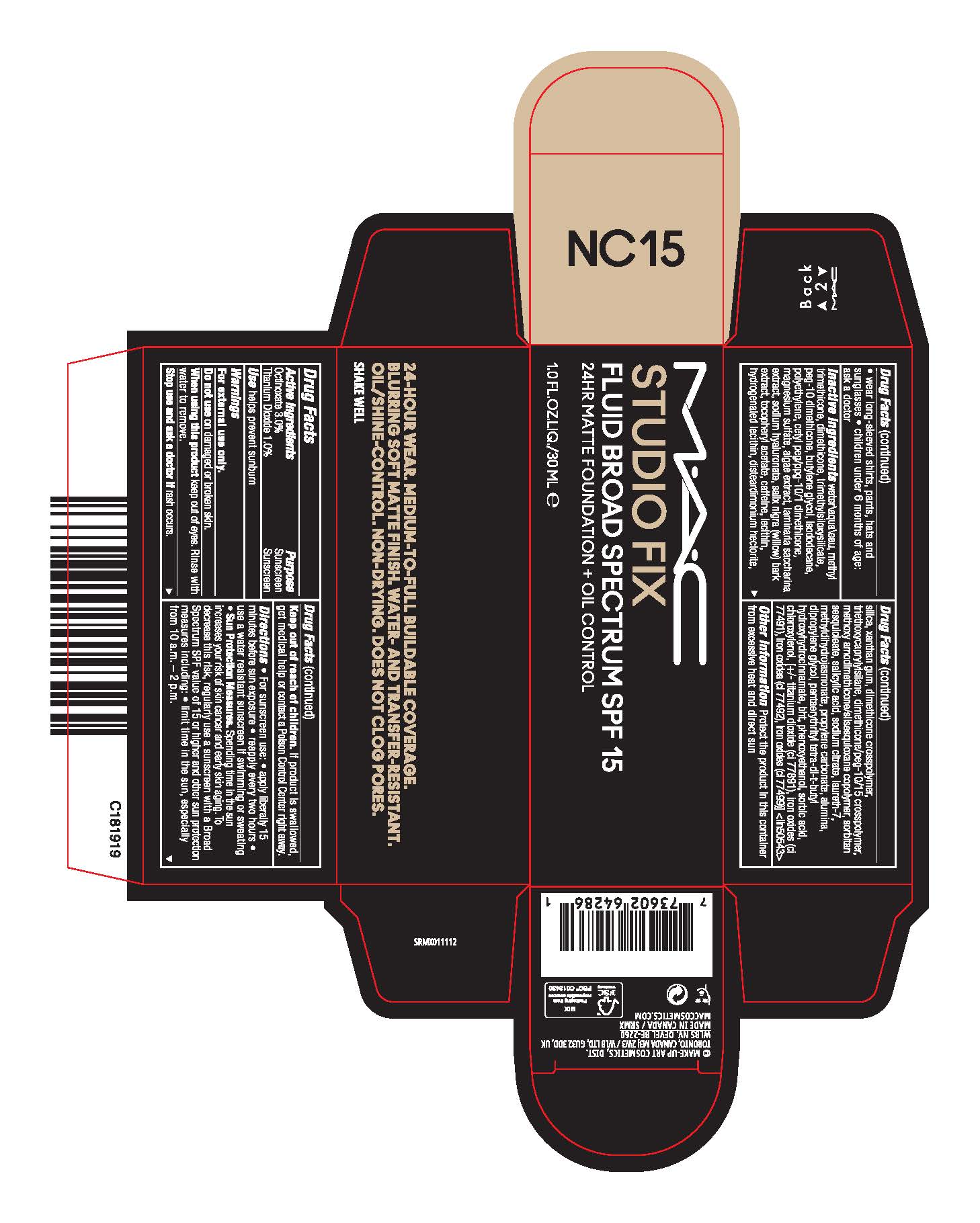 DRUG LABEL: STUDIO FIX FLUID BROAD SPECTRUM SPF 15
NDC: 40046-0082 | Form: EMULSION
Manufacturer: MAKEUP ART COSMETICS
Category: otc | Type: HUMAN OTC DRUG LABEL
Date: 20241217

ACTIVE INGREDIENTS: OCTINOXATE 30 mg/1 mL; TITANIUM DIOXIDE 10 mg/1 mL
INACTIVE INGREDIENTS: HIGH DENSITY POLYETHYLENE; DISTEARDIMONIUM HECTORITE; ALUMINUM OXIDE; WATER; TRIMETHYLSILOXYSILICATE (M/Q 0.6-0.8); ISODODECANE; SACCHARINA LATISSIMA; CHLOROXYLENOL; FERRIC OXIDE YELLOW; MAGNESIUM SULFATE, UNSPECIFIED; PEG-10 DIMETHICONE (600 CST); CETYL PEG/PPG-10/1 DIMETHICONE (HLB 5); PORPHYRIDIUM PURPUREUM; SALIX NIGRA BARK; LECITHIN, SOYBEAN; HYDROGENATED SOYBEAN LECITHIN; DIMETHICONE CROSSPOLYMER (450000 MPA.S AT 12% IN CYCLOPENTASILOXANE); METHYL DIHYDROJASMONATE (SYNTHETIC); SORBIC ACID; XANTHAN GUM; HYALURONATE SODIUM; .ALPHA.-TOCOPHEROL ACETATE; SILICON DIOXIDE; TRIETHOXYCAPRYLYLSILANE; DIMETHICONE/PEG-10/15 CROSSPOLYMER; SORBITAN SESQUIOLEATE; SALICYLIC ACID; SODIUM CITRATE; DIPROPYLENE GLYCOL; FERROSOFERRIC OXIDE; FERRIC OXIDE RED; DIMETHICONE; PROPYLENE CARBONATE; PENTAERYTHRITOL TETRAKIS(3-(3,5-DI-TERT-BUTYL-4-HYDROXYPHENYL)PROPIONATE); CAFFEINE; LAURETH-7; BUTYLATED HYDROXYTOLUENE; PHENOXYETHANOL; METHYL TRIMETHICONE; BUTYLENE GLYCOL

MAC STUDIO FIX FLUID BROAD SPECTRUM SPF 15

Active Ingredients

Octinoxate 3.0%

Titanium Dioxide 1.0%

Purpose

Sunscreen

USE

helps prevent sunburn

WARNINGS

For External use only

Do not use

on damaged or broken skin

When using this product

keep out of eyes, Rinse with water to remove

Stop use and ask a doctor if

rash occurs

Keep out of reach of children

If product is swallowed, get medical help or contact a Poison Control Center right away

Directions

- For sunscreen use:
- apply liberally 15 minutes before sun exposure
- reapply at least every two hours
- use a water resistant sunscreen if swimming or sweating
- Sun Protection Measures. Spending time in the sun increases your risk of skin cancer and early skin aging. To decrease this risk, regularly use a sunscreen with a Broad Spectrum SPF value of 15 or higher and other sun protection measures including:
- limit time in the sun, especially from 10 a.m.–2 p.m.
- wear long-sleeved shirts, pants, hats and sunglasses
- children under 6 months of age: ask a doctor

Inactive Ingredients

WATER\AQUA\EAU,METHYL TRIMETHICONE,DIMETHICONE,TRIMETHYLSILOXYSILICATE,PEG-10 DIMETHICONE,BUTYLENE GLYCOL,ISODODECANE,POLYETHYLENE,CETYL PEG/PPG-10/1 DIMETHICONE,MAGNESIUM SULFATE,ALGAE EXTRACT,LAMINARIA SACCHARINA EXTRACT,SODIUM HYALURONATE,SALIX NIGRA (WILLOW) BARK EXTRACT,TOCOPHERYL ACETATE,CAFFEINE,LECITHIN,HYDROGENATED LECITHIN,DISTEARDIMONIUM HECTORITE,SILICA,XANTHAN GUM,DIMETHICONE CROSSPOLYMER,TRIETHOXYCAPRYLYLSILANE,DIMETHICONE/PEG-10/15 CROSSPOLYMER,METHOXY AMODIMETHICONE/SILSESQUIOXANE COPOLYMER,SORBITAN SESQUIOLEATE,SALICYLIC ACID,SODIUM CITRATE,LAURETH-7,METHYLDIHYDROJASMONATE,PROPYLENE CARBONATE,ALUMINA,DIPROPYLENE GLYCOL,PENTAERYTHRITYL TETRA-DI-T-BUTYL HYDROXYHYDROCINNAMATE,BHT,PHENOXYETHANOL,SORBIC ACID,CHLOROXYLENOL, [+/- TITANIUM DIOXIDE (CI 77891),IRON OXIDES (CI 77491),IRON OXIDES (CI 77492),IRON OXIDES (CI 77499)] <ILN50543>

Other Information

Protect the product in this container from excessive heat and direct sun

PRINCIPAL DISPLAY PANEL

MAC
STUDIO FIX
FLUID BROAD SPECTRUM SPF 15
24 HR MATTE FOUNDATION + OIL CONTROL

1.0 FL.OZ.LIQ/30ML e